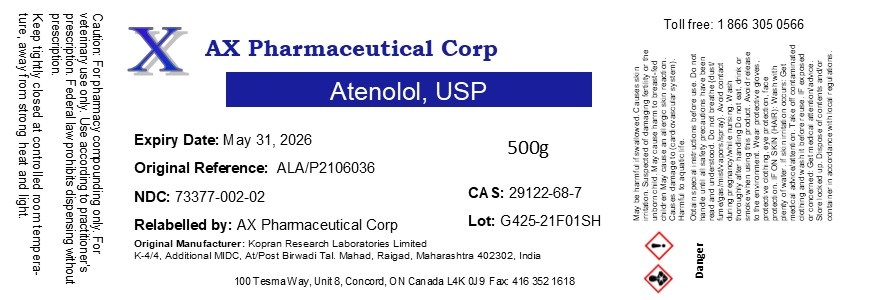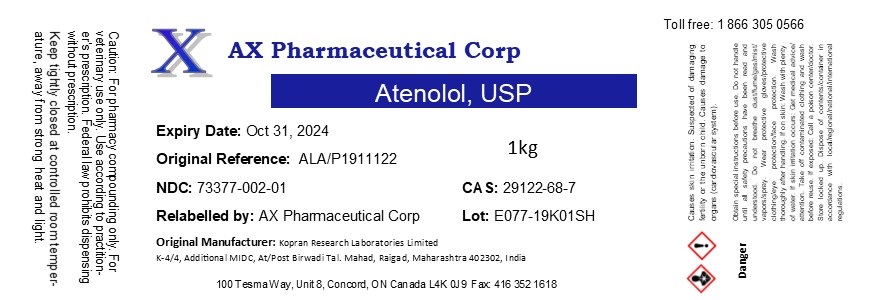 DRUG LABEL: Atenolol
NDC: 73377-002 | Form: POWDER
Manufacturer: AX Pharmaceutical Corp
Category: other | Type: BULK INGREDIENT - ANIMAL DRUG
Date: 20220715

ACTIVE INGREDIENTS: ATENOLOL 1 kg/1 kg

Atenolol